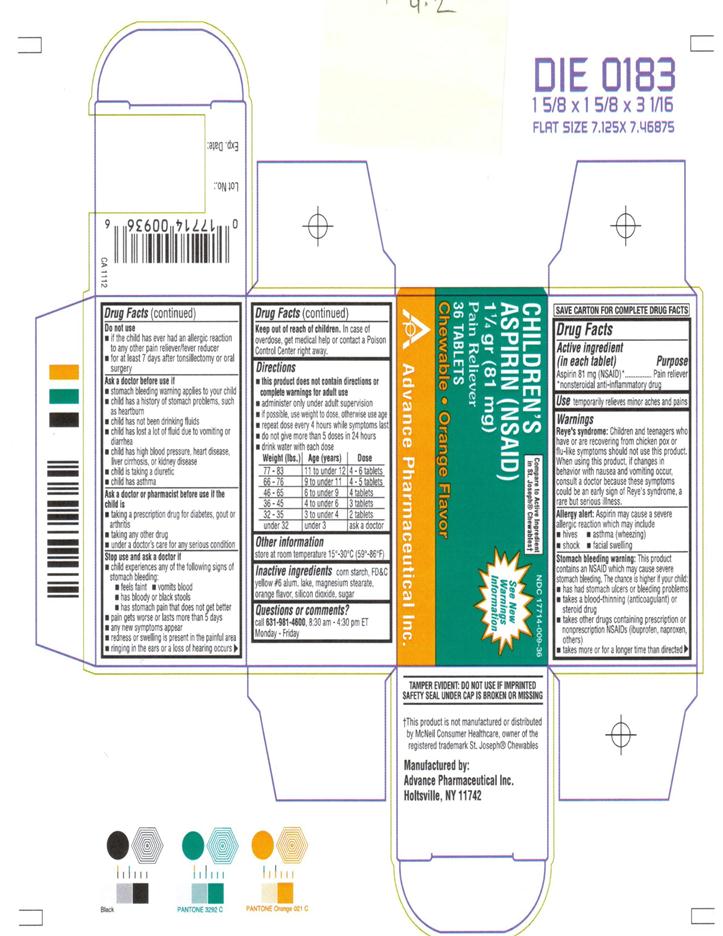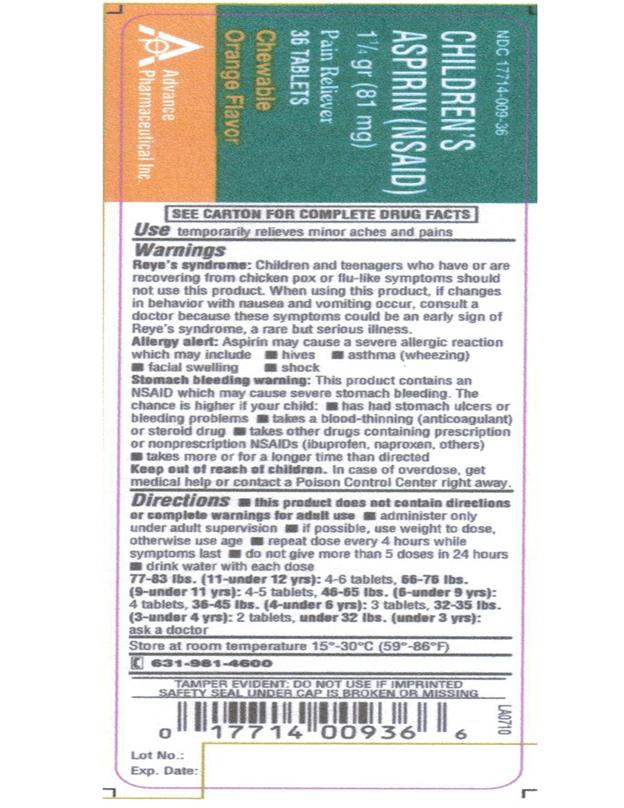 DRUG LABEL: Aspirin
NDC: 17714-009 | Form: TABLET, CHEWABLE
Manufacturer: Advance Pharmaceutical Inc.
Category: otc | Type: HUMAN OTC DRUG LABEL
Date: 20241226

ACTIVE INGREDIENTS: ASPIRIN 81 mg/1 1
INACTIVE INGREDIENTS: STARCH, CORN; FD&C YELLOW NO. 6; MAGNESIUM STEARATE; ORANGE; SILICON DIOXIDE; SUCROSE

ASPIRIN 81mg

Active Ingredient

(in each tablet)

Aspirin 81 mg (NSAID) *

*nonsteroidal anti-inflammatory drug

Purpose

Pain Reliever

Use

- temporarily relieves minor aches and pains
- for other uses, see your doctor, but do not use for more than 10 days without consulting your doctor because serious side effect may occur.

Warnings

Reye’s Syndrome:Children and teenagers who have or are recovering from chicken pox or flu-like symptoms should not use this product. When using this product, if changes in behavior with nausea and vomiting occur, consult a doctor because these symptoms could be an early signs of Reye’s syndrome, a rare but serious illness.

Allergy Alert:Aspirin may cause a severe allergic reaction which may include

- hives
- asthma (wheezing)
- shock
- facial swelling
  Stomach Bleeding Warning:This product contains an NSAID, which may cause severe stomach bleeding. The chance is higher if your child
- has had stomach ulcers or bleeding problems
- take a blood-thinning (anticoagulant) or steroid drug
- takes other drugs containing prescription or nonprescription NSAIDs (ibuprofen, naproxen, others)
- takes more or for a longer time than directed
  Do not use
- if the child has ever had an allergic reaction to any other pain reliever / fever reducer
- for at least 7 days after tonsillectomy or oral surgery
  Ask a doctor before use if
- stomach bleeding warning applies to your child
- child has a history of stomach problems, such as heartburn
- child has not been drinking fluids
- child has lost a lot of fluid due to vomiting and diarrhea
- child has high blood pressure, heart disease, lever cirrhosis, or kidney disease
- child is taking a diuretic
- child has asthma
  Ask a doctor or pharmacist before use if the child is
- taking a prescription drug for diabetes, gout or arthritis
- taking any other drug
- under a doctor’s care for any serious condition
  Stop use and ask a doctor if
- child experiences any of the following signs of stomach bleeding:
- feels faint
- vomits blood
- has bloody or black stools
- has stomach pain that does not get better
- pain gets worse or lasts more than 5 days
- any new symptoms appear
- redness or swelling is present in the painful area
- ringing in the ears or a loss of hearing occurs
  If pregnant or breast-feeding,ask a health professional before use. It is especially important not to use aspirin during the last 3 months of pregnancy unless definitely directed to do so by a doctor because it may cause problems in the unborn child or complications during delivery.

Keep out of reach of children.

In case of overdose, get medical help or contact a Poison Control Center right away.

Directions

- this product does not contain directions or complete warnings for adult use
- administer only under adult supervision
- if possible, use weight to dose, otherwise use age
- repeat dose every 4 hours while symptoms last
- do not give more than 5 doses in 24 hours
- drink water with each dose
  Weight (lbs.) | Age (years) | Dose
  77 – 83 | 11 to under 12 | 4 – 6 tablets
  66 – 76 | 9 to under 11 | 4 - 5 tablets
  46 – 65 | 6 to under 9 | 4 tablets
  36 – 45 | 4 to under 6 | 3 tablets
  32 – 35 | 3 to under 4 | 2 tablets
  under 32 | under 3 | ask a doctor
  DRINK A FULL GLASS OF WATER WITH EACH DOSE
- adults and children 12 years and older :take 4 to 8 tablets every 4 hours while symptoms last, but not more than 48 tablets in 24 hours.
- Children under 12 years:ask a doctor

Other Information

- store at 15-30 °C (59-86 °F)

Inactive Ingredients

corn starch, FD&C Yellow #6 alum. lake, magnesium stearate, orange flavor, silicon dioxide, sugar

Questions or Comments

Call 631-981-4600, 8.30am – 4.30 pm ET Monday-Friday

TAMPER EVIDENT: DO NOT USE IF IMPRINTED SAFETY SEAL UNDER CAP IS BROKEN OR MISSING

Manufactured by: Advance Pharmaceutical, Inc. Holtsville, NY 11742

PACKAGE LABEL.PRINCIPAL DISPLAY PANEL

NDC: 17714-009-36 – 36 COUNT